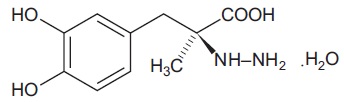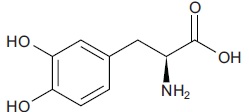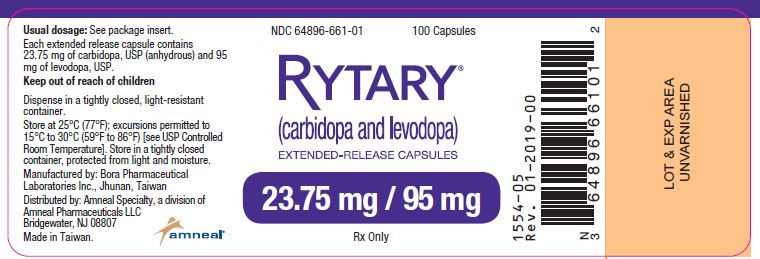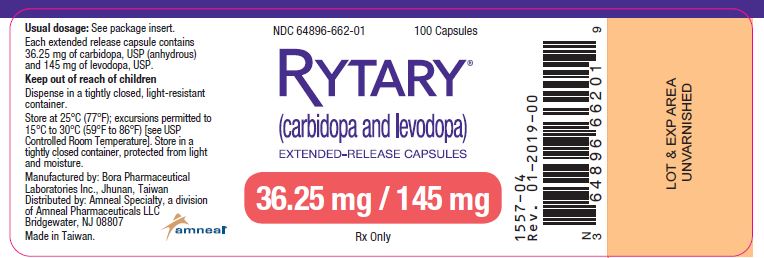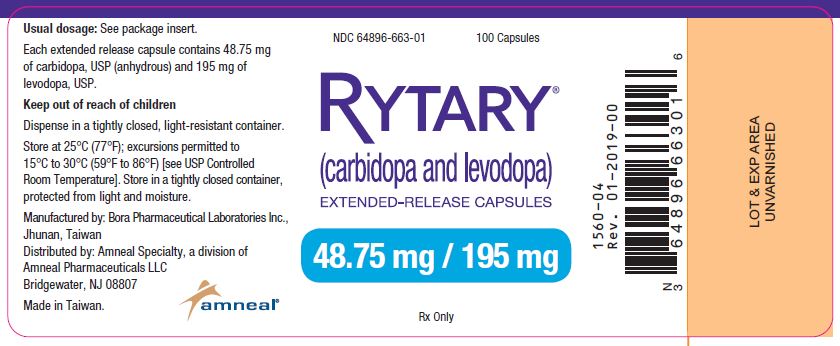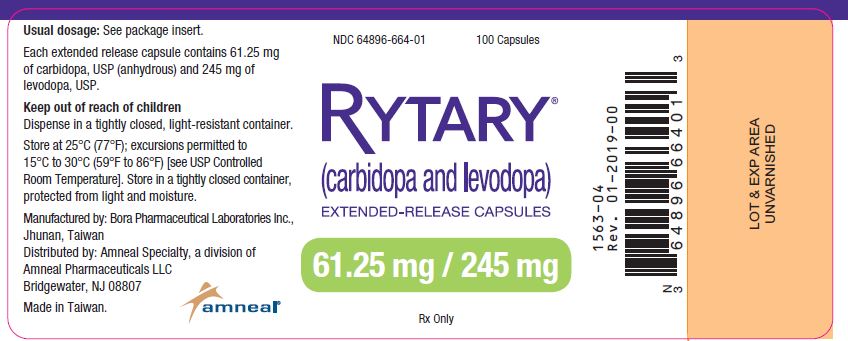 DRUG LABEL: RYTARY
NDC: 64896-661 | Form: CAPSULE, EXTENDED RELEASE
Manufacturer: Amneal Pharmaceuticals LLC
Category: prescription | Type: HUMAN PRESCRIPTION DRUG LABEL
Date: 20250804

ACTIVE INGREDIENTS: LEVODOPA 95 mg/1 1; CARBIDOPA HYDRATE 23.75 mg/1 1
INACTIVE INGREDIENTS: MICROCRYSTALLINE CELLULOSE; MANNITOL; TARTARIC ACID; ETHYLCELLULOSE; HYPROMELLOSE 2910 (6 MPA.S); SODIUM STARCH GLYCOLATE TYPE A POTATO; SODIUM LAURYL SULFATE; POVIDONE; TALC; METHACRYLIC ACID - METHYL METHACRYLATE COPOLYMER (1:1); METHACRYLIC ACID - METHYL METHACRYLATE COPOLYMER (1:2); TRIETHYL CITRATE; CROSCARMELLOSE SODIUM; MAGNESIUM STEARATE; GELATIN; TITANIUM DIOXIDE; FD&C BLUE NO. 2; FERRIC OXIDE YELLOW; BUTYL ALCOHOL; ALCOHOL; ISOPROPYL ALCOHOL; PROPYLENE GLYCOL; SHELLAC; AMMONIA

HIGHLIGHTS OF PRESCRIBING INFORMATION

These highlights do not include all the information needed to use RYTARY safely and effectively. See full prescribing information for RYTARY.
RYTARY (carbidopa and levodopa) extended-release capsules, for oral use
Initial U.S. Approval: 1975

1 INDICATIONS AND USAGE

RYTARY is a combination of carbidopa (an aromatic amino acid decarboxylation inhibitor) and levodopa (an aromatic amino acid) indicated for the treatment of Parkinson's disease, post-encephalitic parkinsonism, and parkinsonism that may follow carbon monoxide intoxication or manganese intoxication. (1)

2 DOSAGE AND ADMINISTRATION

- Levodopa-naïve patients: Starting dose is 23.75 mg/95 mg three times daily; may increase to 36.25 mg/145 mg three times daily on the fourth day of treatment. (2.1)
- See Table 1 for instructions for converting patients taking immediate-release carbidopa-levodopa to an initial dose of RYTARY. Dosages of RYTARY are not interchangeable with other carbidopa-levodopa products. (2.2)
- The maximum recommended daily dose of RYTARY is 612.5 mg/2,450 mg. (2.1, 2.2)
- RYTARY may be taken with or without food; do not chew, divide or crush. (2.4, 12.3)

3 DOSAGE FORMS AND STRENGTHS

Extended-release capsules: Carbidopa and levodopa 23.75 mg/95 mg, 36.25 mg/145 mg, 48.75 mg/195 mg, 61.25 mg/245 mg. (3)

4 CONTRAINDICATIONS

- Nonselective MAO inhibitors. (4)

5 WARNINGS AND PRECAUTIONS

- May cause falling asleep during activities of daily living. (5.1)
- Avoid sudden discontinuation or rapid dose reduction to reduce the risk of withdrawal-emergent hyperpyrexia and confusion. (5.2)
- Cardiovascular Events: Monitor patients with a history of cardiovascular disease. (5.3)
- Hallucinations/Psychosis may occur. (5.4)
- Impulse Control Disorders: Consider dose reduction or stopping RYTARY if occurs. (5.5)
- May cause or exacerbate dyskinesia: Consider dose reduction. (5.6)

6 ADVERSE REACTIONS

- Early Parkinson's disease: Most common adverse reactions (incidence ≥ 5% and greater than placebo) are nausea, dizziness, headache, insomnia, abnormal dreams, dry mouth, dyskinesia, anxiety, constipation, vomiting, and orthostatic hypotension. (6.1)
- Advanced Parkinson's disease: Most common adverse reactions (incidence ≥ 5% and greater than oral immediate-release carbidopa-levodopa) are nausea and headache. (6.1)

To report SUSPECTED ADVERSE REACTIONS, contact Amneal Pharmaceuticals LLC at 1-877-835-5472 or FDA at 1-800-FDA-1088 or www.fda.gov/medwatch.

7 DRUG INTERACTIONS

Iron salts and dopamine D2 antagonists including metoclopramide: May reduce the effectiveness of RYTARY. (7.2, 7.3)

8 USE IN SPECIFIC POPULATIONS

Pregnancy: Based on animal data, may cause fetal harm. (8.1)

FULL PRESCRIBING INFORMATION

1 INDICATIONS AND USAGE

RYTARY is indicated for the treatment of Parkinson's disease, post-encephalitic parkinsonism, and parkinsonism that may follow carbon monoxide intoxication or manganese intoxication.

2 DOSAGE AND ADMINISTRATION

2.1 Dosage in Patients Naïve to Levodopa Therapy

The recommended starting dosage of RYTARY in levodopa-naïve patients is 23.75 mg/95 mg taken orally three times a day for the first 3 days. On the fourth day of treatment, the dosage of RYTARY may be increased to 36.25 mg/145 mg taken three times a day.

Based upon individual patient clinical response and tolerability, the RYTARY dose may be increased up to a maximum recommended dose of 97.5 mg/390 mg taken three times a day. The dosing frequency may be changed from three times a day to a maximum of five times a day if more frequent dosing is needed and if tolerated.

Maintain patients on the lowest dosage required to achieve symptomatic control and to minimize adverse reactions such as dyskinesia and nausea. The maximum recommended daily dose of RYTARY is 612.5 mg/2,450 mg.

2.2 Converting from Immediate-Release Carbidopa-Levodopa to RYTARY

The dosages of other carbidopa and levodopa products are not interchangeable on a 1:1 basis with the dosages of RYTARY.

To convert patients from immediate-release carbidopa-levodopa to RYTARY, first calculate the patient’s current total daily dose of levodopa. The starting total daily dose of RYTARY is as recommended in Table 1.

After conversion, any combination of the four RYTARY dosage strengths can be used to achieve an optimal dosing. Adjust the dose and dosing frequency as necessary to maintain patient tolerance and sufficient symptomatic control. Administration of concomitant Parkinson’s disease medications should remain stable while adjusting the RYTARY dose. In clinical trials, RYTARY was administered in divided doses of three to five times a day. The maximum recommended total daily dose of RYTARY is 612.5 mg/2,450 mg.

For patients currently treated with carbidopa and levodopa plus a catechol-O-methyl transferase (COMT) inhibitor (such as entacapone), the initial total daily dose of levodopa in RYTARY described in Table 1 may need to be increased.

Use of RYTARY in combination with other levodopa products has not been studied.

Table 1: Conversion from Immediate-Release Carbidopa-Levodopa to RYTARY

Total Daily Dose of Levodopa in; Immediate-Release Carbidopa-Levodopa | Recommended Starting Dosage of RYTARY
Total Daily Dose of Levodopa in; Immediate-Release Carbidopa-Levodopa | Total Daily Dose of Levodopa in RYTARY | RYTARY Dosing Regimen
400 mg to 549 mg | 855 mg | 3 capsules RYTARY 23.75 mg/95 mg taken TIDa
550 mg to 749 mg | 1,140 mg | 4 capsules RYTARY 23.75 mg/95 mg taken TID
750 mg to 949 mg | 1,305 mg | 3 capsules RYTARY 36.25 mg/145 mg taken TID
950 mg to 1,249 mg | 1,755 mg | 3 capsules RYTARY 48.75 mg/195 mg taken TID
Equal to or greater than 1,250 mg | 2,340 mg or | 4 capsules RYTARY 48.75 mg/195 mg taken TID or
Equal to or greater than 1,250 mg | 2,205 mg | 3 capsules RYTARY 61.25 mg/245 mg taken TID
a TID: three times a day

2.3 Discontinuation of RYTARY

Avoid sudden discontinuation or rapid dose reduction of RYTARY. The daily dose of RYTARY should be tapered at the time of treatment discontinuation [see Warnings and Precautions (5.2)].

2.4 Administration Information

Swallow RYTARY whole with or without food. A high-fat, high-calorie meal may delay the absorption of levodopa by about 2 hours [see Clinical Pharmacology (12.3)].

Do not chew, divide or crush RYTARY capsules. For patients who have difficulty swallowing intact capsules, administer RYTARY by carefully twisting apart both halves of the capsule. Sprinkle the entire contents of both halves of the capsule on a small amount of applesauce (1 to 2 tablespoons) and consume the mixture immediately. Do not store the drug/food mixture for future use.

3 DOSAGE FORMS AND STRENGTHS

Extended-release capsules:

- 23.75 mg carbidopa and 95 mg levodopa: blue and white capsule imprinted with IPX066 on the capsule cap and 95 on the capsule body.
- 36.25 mg carbidopa and 145 mg levodopa: blue and light blue capsule imprinted with IPX066 on the capsule cap and 145 on the capsule body.
- 48.75 mg carbidopa and 195 mg levodopa: blue and yellow capsule imprinted with IPX066 on the capsule cap and 195 on the capsule body.
- 61.25 mg carbidopa and 245 mg levodopa: blue capsule imprinted with IPX066 on the capsule cap and 245 on the capsule body.

4 CONTRAINDICATIONS

RYTARY is contraindicated in patients:

- Currently taking a nonselective monoamine oxidase (MAO) inhibitor (e.g., phenelzine and tranylcypromine) or have recently (within 2 weeks) taken a nonselective MAO inhibitor. Hypertension can occur if these drugs are used concurrently [see Drug Interactions (7.1)].

5 WARNINGS AND PRECAUTIONS

5.1 Falling Asleep During Activities of Daily Living and Somnolence

Patients treated with levodopa, a component of RYTARY, have reported falling asleep while engaged in activities of daily living, including the operation of motor vehicles, which sometimes resulted in accidents. Although many of these patients reported somnolence while on levodopa, some perceived that they had no warning signs (sleep attack), such as excessive drowsiness, and believed that they were alert immediately prior to the event. Some of these events have been reported more than 1 year after initiation of treatment.

It has been reported that falling asleep while engaged in activities of daily living usually occurs in a setting of pre-existing somnolence, although patients may not give such a history. For this reason, prescribers should reassess patients for drowsiness or sleepiness in RYTARY-treated patients, especially since some of the events occur well after the start of treatment. Prescribers should also be aware that patients may not acknowledge drowsiness or sleepiness until directly questioned about drowsiness or sleepiness during specific activities.

Before initiating treatment with RYTARY, advise patients of the potential to develop drowsiness and specifically ask about factors that may increase the risk for somnolence with RYTARY such as concomitant sedating medications or the presence of a sleep disorder. Consider discontinuing RYTARY in patients who report significant daytime sleepiness or episodes of falling asleep during activities that require active participation (e.g., conversations, eating, etc.).

If a decision is made to continue RYTARY, patients should be advised not to drive and to avoid other potentially dangerous activities that might result in harm if the patients become somnolent. There is insufficient information to establish that dose reduction will eliminate episodes of falling asleep while engaged in activities of daily living.

5.2 Withdrawal-Emergent Hyperpyrexia and Confusion

A symptom complex that resembles neuroleptic malignant syndrome (characterized by elevated temperature, muscular rigidity, altered consciousness, and autonomic instability), with no other obvious etiology, has been reported in association with rapid dose reduction, withdrawal of, or changes in dopaminergic therapy. Avoid sudden discontinuation or rapid dose reduction in patients taking RYTARY. If the decision is made to discontinue RYTARY, the dose should be tapered to reduce the risk of hyperpyrexia and confusion [see Dosage and Administration (2.4)].

5.3 Cardiovascular Ischemic Events

Cardiovascular ischemic events have occurred in patients taking RYTARY. In a placebo controlled clinical study in patients with early Parkinson's disease, 7/289 (2.4%) of RYTARY-treated patients experienced cardiovascular ischemic adverse reactions compared to 1/92 (1.1%) of placebo-treated patients. In an active-controlled clinical study in patients with advanced Parkinson's disease, 3/450 (0.7%) of RYTARY-treated patients experienced cardiovascular ischemic adverse reactions compared to 0/471 oral immediate-release carbidopa-levodopa-treated patients. These patients all had a previous history of ischemic heart disease or risk factors for ischemic heart disease.

In patients with a history of myocardial infarction who have residual atrial, nodal, or ventricular arrhythmias, cardiac function should be monitored in an intensive cardiac care facility during the period of initial dosage adjustment.

5.4 Hallucinations/Psychosis

There is an increased risk for hallucinations and psychosis in patients taking RYTARY. In a controlled clinical trial in patients with advanced Parkinson's disease, 9/201 (4%) of RYTARY-treated patients reported hallucinations or psychosis compared to 2/192 (1%) of oral immediate-release carbidopa-levodopa-treated patients.

Hallucinations present shortly after the initiation of therapy and may be responsive to dose reduction in levodopa. Hallucinations may be accompanied by confusion, insomnia, and excessive dreaming. Abnormal thinking and behavior may present with one or more symptoms, including paranoid ideation, delusions, hallucinations, confusion, psychotic-like behavior, disorientation, aggressive behavior, agitation, and delirium.

Because of the risk of exacerbating psychosis, patients with a major psychotic disorder should not be treated with RYTARY. In addition, medications that antagonize the effects of dopamine used to treat psychosis may exacerbate the symptoms of Parkinson's disease and may decrease the effectiveness of RYTARY [see Drug Interactions (7.2)].

5.5 Impulse Control/Compulsive Behaviors

Case reports suggest that patients can experience intense urges to gamble, increased sexual urges, intense urges to spend money, binge eating, and/or other intense urges, and the inability to control these urges while taking one or more of the medications, including RYTARY, that increase central dopaminergic tone and that are generally used for the treatment of Parkinson's disease. In some cases, although not all, these urges were reported to have stopped when the dose was reduced or the medication was discontinued.

Because patients may not recognize these behaviors as abnormal, it is important for prescribers to specifically ask patients or their caregivers about the development of new or increased gambling urges, sexual urges, uncontrolled spending or other urges while being treated with RYTARY. Consider a dose reduction or stopping the medication if a patient develops such urges while taking RYTARY.

5.6 Dyskinesia

RYTARY can cause dyskinesias that may require a dosage reduction of RYTARY or other medications used for the treatment of Parkinson's disease.

5.7 Peptic Ulcer Disease

Treatment with RYTARY may increase the possibility of upper gastrointestinal hemorrhage in patients with a history of peptic ulcer.

5.8 Glaucoma

RYTARY may cause increased intraocular pressure in patients with glaucoma. Monitor intraocular pressure in patients with glaucoma after starting RYTARY.

6 ADVERSE REACTIONS

The following serious adverse reactions are discussed below and elsewhere in the labeling:

- Falling Asleep During Activities of Daily Living and Somnolence [see Warnings and Precautions (5.1)]
- Withdrawal-Emergent Hyperpyrexia and Confusion [see Warnings and Precautions (5.2)]
- Cardiovascular Ischemic Events [see Warnings and Precautions (5.3)]
- Hallucinations/Psychosis [see Warnings and Precautions (5.4)]
- Impulse Control/Compulsive Behaviors [see Warnings and Precautions (5.5)]
- Dyskinesia [see Warnings and Precautions (5.6)]
- Peptic Ulcer Disease [see Warnings and Precautions (5.7)]
- Glaucoma [see Warnings and Precautions (5.8)]

6.1 Clinical Trials Experience

Because clinical trials are conducted under widely varying conditions, adverse reaction rates observed in the clinical trials of a drug cannot be directly compared to rates in the clinical trials of another drug and may not reflect the rates observed in clinical practice.

The safety population consisted of a total of 978 Parkinson’s disease patients who received at least one dose of RYTARY, and had an average duration of exposure of 40 weeks.

Adverse Reactions in Early Parkinson’s Disease

In a placebo-controlled clinical study in patients with early Parkinson’s disease (Study 1), the most common adverse reactions with RYTARY (in at least 5% of patients and more frequently than in placebo) were nausea, dizziness, headache, insomnia, abnormal dreams, dry mouth, dyskinesia, anxiety, constipation, vomiting, and orthostatic hypotension.

Table 2 lists adverse reactions occurring in at least 5% of RYTARY-treated patients and at a higher rate than placebo in Study 1.

Table 2: Adverse Reactions in Study 1 in Patients with Early Stage Parkinson’s Disease

 | Placebo | RYTARY 36.25 mg Carbidopa 145 mg Levodopa TID | RYTARY 61.25 mg Carbidopa 245 mg Levodopa TID | RYTARY 97.5 mg Carbidopa 390 mg Levodopa TID
 | (N=92) % | (N=87) % | (N=104) % | (N=98) %
Nausea | 9 | 14 | 19 | 20
Dizziness | 5 | 9 | 19 | 12
Headache | 11 | 7 | 13 | 17
Insomnia | 3 | 2 | 9 | 6
Abnormal Dreams | 0 | 2 | 6 | 5
Dry Mouth | 1 | 3 | 2 | 7
Dyskinesia | 0 | 2 | 4 | 5
Anxiety | 0 | 2 | 3 | 5
Constipation | 1 | 2 | 6 | 2
Vomiting | 3 | 2 | 2 | 5
Orthostatic Hypotension | 1 | 1 | 1 | 5

Adverse Reactions Leading to Discontinuation in Study 1

In Study 1, 12% of patients discontinued RYTARY early due to adverse reactions; a higher proportion of patients in the 61.25 mg/245 mg RYTARY-treated group (14%) and in the 97.5 mg/390 mg RYTARY-treated group (15%) experienced adverse reactions leading to early discontinuation compared to (4%) in the placebo group. The most common adverse reactions resulting in early discontinuation were nausea, dizziness, and vomiting.

Adverse Reactions in Advanced Parkinson’s Disease

In an active-controlled clinical study in patients with advanced Parkinson’s disease (Study 2), the most common adverse reactions with RYTARY that occurred during dose conversion or maintenance (in at least 5% of patients and more frequently than on oral immediate-release carbidopa-levodopa) were nausea and headache.

Table 3 lists adverse reactions occurring in at least 5% of RYTARY-treated patients and at a higher rate than oral immediate-release carbidopa-levodopa in Study 2.

Table 3: Adverse Reactions in Study 2 in Patients with Advanced Parkinson’s Disease

 | RYTARY (N=201) |  | Immediate-Release Carbidopa-Levodopa (N=192)
Period | Dose Conversiona % | Maintenance % | Dose Conversiona % | Maintenance %
Nausea | 4 | 3 | 6 | 2
Headache | 5 | 1 | 3 | 2
a All patients were converted to RYTARY in the open-label Dose Conversion period and then received randomized treatment during maintenance.

Adverse Reactions Leading to Discontinuation in Study 2

In Study 2, 5% of patients discontinued treatment due to adverse reactions during conversion to RYTARY. The common adverse reactions leading to discontinuation during dose conversion were dyskinesia, anxiety, dizziness, and on and off phenomenon.

6.2 Post-marketing Experience

The following adverse reactions have been identified during post approval use of RYTARY. Because these reactions are reported voluntarily from a population of unknown size, it is not always possible to reliably estimate their frequency or establish causal relationship to RYTARY exposure.

Psychiatric: Suicide attempt, suicidal ideation.

7 DRUG INTERACTIONS

7.1 Monoamine Oxidase (MAO) Inhibitors

The use of nonselective MAO inhibitors with RYTARY is contraindicated [see Contraindications (4)]. Discontinue use of any nonselective MAO inhibitors at least two weeks prior to initiating RYTARY.

The use of selective MAO-B inhibitors (e.g., rasagiline and selegiline) with RYTARY may be associated with orthostatic hypotension. Monitor patients who are taking these drugs concurrently.

7.2 Dopamine D2 Receptor Antagonists and Isoniazid

Dopamine D2 receptor antagonists (e.g., phenothiazines, butyrophenones, risperidone, metoclopramide) and isoniazid may reduce the effectiveness of levodopa. Monitor patients for worsening Parkinson's symptoms.

7.3 Iron Salts

Iron salts or multivitamins containing iron salts can form chelates with levodopa and carbidopa and can cause a reduction in the bioavailability of RYTARY. If iron salts or multivitamins containing iron salts are co-administered with RYTARY, monitor patients for worsening Parkinson's symptoms.

8 USE IN SPECIFIC POPULATIONS

8.1 Pregnancy

Risk Summary

There are no adequate data on the developmental risk associated with the use of RYTARY in pregnant women. In animal studies, carbidopa-levodopa has been shown to be developmentally toxic (including teratogenic effects) at clinically relevant doses (see Data).

The estimated background risk of major birth defects and miscarriage in the indicated population is unknown. In the U.S. general population, the estimated background risk of major birth defects and miscarriage in clinically recognized pregnancies is 2% to 4% and 15% to 20%, respectively.

Data

Animal Data

When administered to pregnant rabbits throughout organogenesis, carbidopa-levodopa caused both visceral and skeletal malformation in fetuses at all doses and ratios of carbidopa-levodopa tested. No teratogenic effects were observed when carbidopa-levodopa was administered to pregnant mice throughout organogenesis.

There was a decrease in the number of live pups delivered by rats receiving carbidopa-levodopa during organogenesis.

8.2 Lactation

Risk Summary

Levodopa has been detected in human milk after administration of carbidopa-levodopa. There are no data on the presence of carbidopa in human milk, the effects of levodopa or carbidopa on the breastfed infant, or the effects on milk production. However, inhibition of lactation may occur because levodopa decreases secretion of prolactin in humans. Carbidopa is excreted in rat milk.

The developmental and health benefits of breastfeeding should be considered along with the mother’s clinical need for RYTARY and any potential adverse effects on the breastfed infant from RYTARY or from the underlying maternal condition.

8.4 Pediatric Use

Safety and effectiveness in pediatric patients have not been established.

8.5 Geriatric Use

In controlled clinical trials of RYTARY, 418 patients were 65 years or older and no overall differences in safety and efficacy were observed between these patients and those under 65 years of age.

10 OVERDOSAGE

In the active-controlled clinical study, a patient accidentally ingested 4.68 grams of carbidopa/18.7 grams of levodopa contained in RYTARY over a 2-day period. The patient experienced acute psychosis and dyskinesias. The patient recovered and completed the study on a reduced dose of RYTARY.

Based on the limited available information, the acute symptoms of levodopa/dopa decarboxylase inhibitor overdosage can be expected to arise from dopaminergic overstimulation. Doses of a few grams may result in CNS disturbances, with an increasing likelihood of cardiovascular disturbance (e.g., hypotension, tachycardia) and more severe psychiatric problems at higher doses. An isolated report of rhabdomyolysis and another of transient renal insufficiency suggest that levodopa overdosage may give rise to systemic complications, secondary to dopaminergic overstimulation.

Monitor patients and provide supportive care. Patients should receive electrocardiographic monitoring for the development of arrhythmias; if needed, appropriate antiarrhythmic therapy should be given. The possibility that the patient may have taken other drugs, increasing the risk of drug interactions (especially catechol-structured drugs) should be taken into consideration.

11 DESCRIPTION

RYTARY is a combination of carbidopa, an inhibitor of aromatic amino acid decarboxylation, and levodopa, an aromatic amino acid, in extended-release capsules for oral use.

Carbidopa is a white to creamy white powder, slightly soluble in water, with a molecular weight of 244.2. It is designated chemically as (-)-L-α-hydrazino-3, 4-dihydroxy-α-methylhydrocinnamic acid monohydrate. Its molecular formula is C10H14N2O4 • H2O and its structural formula is:

Capsule content is expressed in terms of anhydrous carbidopa, which has a molecular weight of 226.2.

Levodopa is a white to off-white, crystalline powder, slightly soluble in water, with a molecular weight of 197.2. It is designated chemically as (−)-3-(3, 4-Dihydroxyphenyl)-L-alanine. Its molecular formula is C9H11NO4 and its structural formula is:

Each extended-release capsule contains 23.75 mg carbidopa, USP and 95 mg levodopa USP, 36.25 mg carbidopa, USP and 145 mg levodopa USP, 48.75 mg carbidopa, USP and 195 mg levodopa USP, or 61.25 mg carbidopa, USP and 245 mg levodopa USP. The inactive ingredients are microcrystalline cellulose, mannitol, tartaric acid, ethyl cellulose, hypromellose, sodium starch glycolate, sodium lauryl sulfate, povidone, talc, methacrylic acid copolymers, triethyl citrate, croscarmellose sodium, and magnesium stearate.

All capsule shells contain gelatin and titanium dioxide. In addition, all blue capsule shells contain FD&C Blue #2 and yellow iron oxide. All yellow capsule shells contain yellow iron oxide.

All capsules imprinted with blue pharmaceutical ink contain FD&C Blue #2, butyl alcohol, dehydrated alcohol, isopropyl alcohol, propylene glycol, shellac and strong ammonia solution.

12 CLINICAL PHARMACOLOGY

12.1 Mechanism of Action

Carbidopa

When levodopa is administered orally, it is rapidly decarboxylated to dopamine in extracerebral tissues so that only a small portion of a given dose is transported unchanged to the central nervous system. Carbidopa inhibits the decarboxylation of peripheral levodopa, making more levodopa available for delivery to the brain.

Levodopa

Levodopa is the metabolic precursor of dopamine, does cross the blood-brain barrier, and presumably is converted to dopamine in the brain. This is thought to be the mechanism whereby levodopa relieves symptoms of Parkinson's disease.

12.2 Pharmacodynamics

Because its decarboxylase inhibiting activity is limited to extracerebral tissues, administration of carbidopa with levodopa makes more levodopa available to the brain. The addition of carbidopa to levodopa reduces the peripheral effects (nausea, vomiting) due to decarboxylation of levodopa; however, carbidopa does not decrease the adverse reactions due to the central effects of levodopa.

Patients treated with levodopa therapy for Parkinson's disease may develop motor fluctuations characterized by end-of-dose failure, peak dose dyskinesia, ‘on-off’ phenomenon, and akinesia.

12.3 Pharmacokinetics

Absorption

Carbidopa

Following oral dosing of RYTARY the maximum concentration occurred at approximately 3 hours. The bioavailability of carbidopa from RYTARY relative to immediate-release carbidopa-levodopa tablets was approximately 50%.

Levodopa

The pharmacokinetics of RYTARY were evaluated following single-doses in healthy subjects and following single- and multiple-doses in patients with Parkinson’s disease. The bioavailability of levodopa from RYTARY in patients was approximately 70% relative to immediate-release carbidopa-levodopa. For comparable doses, RYTARY results in a levodopa peak concentration (Cmax) that is 30% that of immediate-release carbidopa-levodopa. Following an initial peak at about one hour, plasma concentrations are maintained for about 4 to 5 hours before declining.

In patients with Parkinson’s disease, multiple-dose pharmacokinetics was comparable to single-dose pharmacokinetics, i.e., there was minimal accumulation of levodopa. Variation in levodopa peak to trough plasma concentrations at steady-state defined as (Cmax-Cmin)/Cavg was approximately 1.5 for RYTARY compared to approximately 3.2 for immediate-release levodopa.

Distribution

Carbidopa is approximately 36% bound to plasma proteins. Approximately 10% to 30% of levodopa is bound to plasma protein.

Metabolism and Elimination

Carbidopa

The terminal phase elimination half-life of carbidopa is approximately 2 hours.

Carbidopa is metabolized to two main metabolites: α-methyl-3-methoxy-4-hydroxyphenylpropionic acid and α-methyl-3,4-dihydroxy-phenylpropionic acid. These two metabolites are primarily eliminated in the urine unchanged or as a glucuronide. Unchanged carbidopa accounts for 30% of the total urinary excretion.

Peripheral dopa-decarboxylase may be saturated by carbidopa in other carbidopa-levodopa products at 70 mg per day to 100 mg per day, which produces equivalent exposure to 140 mg to 200 mg of carbidopa provided by RYTARY.

Levodopa

The terminal phase elimination half-life of levodopa, the active moiety of antiparkinsonian activity, is approximately 2 hours in the presence of carbidopa.

Levodopa is extensively metabolized to various metabolites. The two major metabolic pathways are decarboxylation by dopa decarboxylase (DDC) and O-methylation by catechol-O-methyltransferase (COMT).

Dose Proportionality

RYTARY shows approximately dose proportional pharmacokinetics for both carbidopa and levodopa over the levodopa dosage strength range of 95 mg to 245 mg.

Effect of Food

In healthy adults, oral administration of RYTARY after a high-fat, high-calorie meal reduced Cmax approximately 21% and increased AUCinf approximately 13% for levodopa compared to administration in the fasted state. There may be a delay by 2 hours in the absorption of levodopa when RYTARY is taken with a high-fat, high-calorie meal. In addition, absorption of levodopa may be decreased by a high protein meal.

Specific Populations

Elderly

In pharmacokinetics studies following a single-dose of RYTARY, the peak concentrations of carbidopa and levodopa are generally similar between younger (45 to 60 years) and older (60 to 75 years) subjects.

Gender

In pharmacokinetics studies following a single-dose of RYTARY:

- Carbidopa

At comparable doses females are reported to have higher carbidopa peak concentrations and systemic exposure (approximately 33%) compared to males. Median time to peak concentration and terminal half-life are comparable between males and females.

- Levodopa

At comparable doses females are reported to have higher levodopa peak concentrations (approximately 23% to 33%) and systemic exposure (approximately 33% to 37%) compared to males. Median time to peak concentration and terminal half-life are comparable between males and females.

13 NONCLINICAL TOXICOLOGY

13.1 Carcinogenesis, Mutagenesis, Impairment of Fertility

Carcinogenesis

In rats, oral administration of carbidopa-levodopa for two years resulted in no evidence of carcinogenicity.

Mutagenesis

Carbidopa was mutagenic in the in vitro Ames test and in the in vitro mouse lymphoma tk assay but was negative in the in vivo mouse micronucleus assay.

Impairment of Fertility

In reproduction studies, no effects on fertility were observed in rats receiving carbidopa-levodopa.

14 CLINICAL STUDIES

14.1 Patients with Early Parkinson's Disease

The effectiveness of RYTARY in patients with early Parkinson’s disease was established in a randomized, double-blind, placebo-controlled, fixed-dose, parallel-group, 30-week clinical trial (Study 1). Patients enrolled in Study 1 (n=381) were Hoehn and Yahr Stage I–III with a median disease duration of 1 year, and had limited or no prior exposure to levodopa and dopamine agonists. Patients continued taking concomitant selective monoamine oxidase B (MAO-B) inhibitors, amantadine, and anticholinergics provided the doses were stable for at least 4 weeks before screening. Eligible patients were randomized (1:1:1:1) to placebo or one of three fixed doses of RYTARY (carbidopa/levodopa doses of 36.25 mg/145 mg, 61.25 mg/245 mg, or 97.5 mg/390 mg, three times a day). Patients were not allowed to receive supplemental levodopa or catechol-O-methyl transferase (COMT) inhibitors. Patients receiving RYTARY initiated treatment at 23.75 mg/95 mg three times daily (TID). The dose was increased on Day 4 and the maximum study dose (97.5 mg/390 mg TID) was achieved by Day 22.

The clinical outcome measure in Study 1 was the mean change from baseline in the sum of the Unified Parkinson’s Disease Rating Scale (UPDRS) Part II (activities of daily living) score, and UPDRS Part III (motor score) for RYTARY, compared to placebo at Week 30 (or early termination). The mean score decrease (i.e., improvement) from baseline to Week 30 for each of the three RYTARY dosage groups was significantly greater than for placebo. The results of Study 1 are shown in Table 4.

Table 4: Study 1: Change from Baseline in UPDRS Part II plus Part III Score at Week 30 (or at Early Termination) in Levodopa-Naïve Patients with Early Parkinson’s Disease

Treatment | Mean UPDRS (Part II and Part III) Scorea
Treatment | Baselineb | Week 30 | Change from Baseline at Week 30c
Placebo | 36.5 | 35.9 | −0.6
RYTARY 36.25 mg/145 mg TID | 36.1 | 24.4 | −11.7d
RYTARY 61.25 mg/245 mg TID | 38.2 | 25.3 | −12.9d
RYTARY 97.5 mg/390 mg TID | 36.3 | 21.4 | −14.9d
a For the UPDRS, higher scores indicate greater severity of impairment.
b All values based on 361 patients who had valid End-of-Study values.
c Negative numbers indicate improvement as compared with the baseline value.
d P-value is less than 0.05.

14.2 Patients with Advanced Parkinson's Disease

Study 2 was a 22-week trial consisting of a 3-week dose adjustment of current levodopa treatment prior to a 6-week conversion to RYTARY, which was followed by a 13-week, randomized, multicenter, double-blind, levodopa-containing active control, double-dummy, parallel group trial. The study enrolled 471 (393 randomized) patients (Hoehn & Yahr Stages I-IV) who had been maintained on a stable regimen of at least 400 mg per day of levodopa prior to entry into the trial. Patients were continued on concomitant dopamine agonists, selective monoamine oxidase B (MAO-B) inhibitors, amantadine, and anticholinergics provided the doses were stable for at least 4 weeks prior to screening. Patients were randomized to receive either RYTARY or immediate-release carbidopa-levodopa at the dose determined during the adjustment or conversion phases. Patients were not allowed to receive supplemental carbidopa-levodopa or catechol-O-methyl transferase (COMT) inhibitor products during the trial.

In Study 2, approximately 60% of patients required further up titration and approximately 16% of patients required down titration compared to the recommended starting dose of RYTARY. The final total daily dose of levodopa from RYTARY was approximately double that of the final total daily dose of levodopa from immediate-release tablets. The majority (88%) of patients in Study 2 received less than 2,400 mg; the median dose was 1,365 mg.

The clinical outcome measure in Study 2 was the percentage of “off” time during waking hours at Week 22 (or at early termination), as assessed by the patient’s Parkinson’s Disease Diary. The “off” time was significantly improved in RYTARY-treated patients compared to immediate-release carbidopa-levodopa-treated patients (Table 5). The decrease in “off” time observed with RYTARY occurred with a concomitant increase in “on time” without troublesome dyskinesia.

Table 5: Study 2: Parkinson’s Disease Diary Measures in Patients with Advanced Parkinson’s Disease

Percentage of waking hours spent in “Off” | Baseline | Week 22 (or Early Termination)
RYTARY | 36.9% | 23.8%a
Immediate-release carbidopa-levodopa | 36.0% | 29.8%
“Off” Time (hours)
RYTARY | 6.1 hours | 3.9 hoursa
Immediate-release carbidopa-levodopa | 5.9 hours | 4.9 hours
“On” Time with no or non-troublesome dyskinesia (hours)
RYTARY | 10.0 hours | 11.8 hoursa
Immediate-release carbidopa-levodopa | 10.1 hours | 10.9 hours
a P-value is less than 0.05.

16 HOW SUPPLIED/STORAGE AND HANDLING

16.1 How Supplied

RYTARY (carbidopa and levodopa) Extended-Release Capsules are available in the following strengths:

- 23.75 mg Carbidopa and 95 mg of Levodopa: blue and white capsule imprinted with IPX066 on the capsule cap and 95 on the capsule body.
  They are available as follows:
  Bottles of 100: (NDC 64896-661-01)
  Bottles of 240: (NDC 64896-661-43)
- 36.25 mg Carbidopa and 145 mg Levodopa: blue and light blue capsule imprinted with IPX066 on the capsule cap and 145 on the capsule body.
  They are available as follows:
  Bottles of 100: (NDC 64896-662-01)
  Bottles of 240: (NDC 64896-662-43)
- 48.75 mg Carbidopa and 195 mg Levodopa: blue and yellow capsule imprinted with IPX066 on the capsule cap and 195 on the capsule body.
  They are available as follows:
  Bottles of 100: (NDC 64896-663-01)
  Bottles of 240: (NDC 64896-663-43)
- 61.25 mg Carbidopa and 245 mg Levodopa: blue capsule imprinted with IPX066 on the capsule cap and 245 on the capsule body.
  They are available as follows:
  Bottles of 100: (NDC 64896-664-01)
  Bottles of 240: (NDC 64896-664-43)

16.2 Storage and Handling

Store at 20°C to 25°C (68°F to 77°F); excursions permitted between 15°C to 30°C (59°F to 86°F) [see USP Controlled Room Temperature]. Store in a tightly closed container, protected from light and moisture.

Dispense in a tightly closed, light-resistant container.

17 PATIENT COUNSELING INFORMATION

Dosing Instructions

- Advise patients to not take other carbidopa-levodopa preparations with RYTARY without consulting their healthcare provider [see Dosage and Administration (2.2)].
- Advise patients to call their healthcare provider before stopping RYTARY. Discontinue RYTARY slowly. Tell patients to call their healthcare provider if they develop withdrawal symptoms such as fever, confusion or severe muscle stiffness [see Dosage and Administration (2.3) and Warnings and Precautions (5.2)].
- Advise patients to swallow RYTARY capsules whole, without chewing, dividing, or crushing [see Dosage and Administration (2.4)].
- For patients with difficulty swallowing, the entire contents of the RYTARY capsule may be sprinkled on 1 to 2 tablespoons of applesauce and should be taken immediately [see Dosage and Administration (2.4)].

- Inform patients that a high fat, high calorie meal may delay the absorption of levodopa and the onset of action by 2 to 3 hours. For this reason, consideration should be given to taking the first dose of the day about 1 to 2 hours before eating [see Dosage and Administration (2.4) and Clinical Pharmacology (12.3)].

Falling Asleep

Advise patients that certain side effects such as sleepiness and dizziness that have been reported with RYTARY may affect some patients’ ability to drive and operate machinery safely [see Warnings and Precautions (5.1) and Adverse Reactions (6.1)].

Suicide Attempt and Suicidal Ideation

Instruct patients, family members and caregivers to notify their healthcare provider if suicide attempt and/or suicidal ideation are experienced by patients using RYTARY [see Adverse Reactions (6.2)].

Hallucinations and Psychosis

Inform patients that hallucinations can occur with levodopa products [see Warnings and Precautions (5.4)].

Impulse Control Disorder

Inform patients of the potential for experiencing intense urges to gamble, increased sexual urges, and other intense urges and the inability to control these urges while taking one or more of the medications that increase central dopaminergic tone, that are generally used for the treatment of Parkinson’s disease [see Warnings and Precautions (5.5)].

Dyskinesia

Instruct patients to notify their healthcare provider if abnormal involuntary movements appear or get worse during treatment with RYTARY [see Warnings and Precautions (5.6)].

Hypotension and Syncope

Advise patients that they may develop orthostatic hypotension with or without symptoms such as dizziness, nausea, syncope, and sweating [see Adverse Reactions (6.1)]. Advise patients to rise slowly after sitting or lying down, especially if they have been doing so for a prolonged period.

Advise patients of the possible additive sedative effects when taking other CNS depressants in combination with RYTARY.

Pregnancy and Breastfeeding

Advise patients to notify their healthcare provider if they become pregnant or intend to become pregnant during RYTARY therapy [see Use in Specific Populations (8.1)].

Advise female patients to notify their physicians if they intend to breastfeed or are breastfeeding an infant [see Use in Specific Populations (8.2)].

Manufactured by:

Bora Pharmaceutical Laboratories Inc.

Jhunan, Taiwan

Distributed by:

Amneal Specialty, a division of Amneal Pharmaceuticals LLC

Bridgewater, NJ 08807

Printed in USA

Copyright 2019 Amneal Pharmaceuticals LLC

All rights reserved

Rev. 08-2025-01

1566-05

PRINCIPAL DISPLAY PANEL - 23.75 mg/95 mg Capsule Bottle Label

NDC 64896-661-01

RYTARY® (Carbidopa and Levodopa) Extended-Release Capsules

23.75 mg/95 mg

100 Capsules

Rx Only

Amneal Specialty, a division of Amneal Pharmaceuticals LLC

PRINCIPAL DISPLAY PANEL - 36.25 mg/145 mg Capsule Bottle Label

NDC 64896-662-01

RYTARY® (Carbidopa and Levodopa) Extended-Release Capsules

36.25 mg/145 mg

100 Capsules

Rx Only

Amneal Specialty, a division of Amneal Pharmaceuticals LLC

PRINCIPAL DISPLAY PANEL - 48.75 mg/195 mg Capsule Bottle Label

NDC 64896-663-01

RYTARY® (Carbidopa and Levodopa) Extended-Release Capsules

48.75 mg/195 mg

100 Capsules

Rx Only

Amneal Specialty, a division of Amneal Pharmaceuticals LLC

PRINCIPAL DISPLAY PANEL - 61.25 mg/245 mg Capsule Bottle Label

NDC 64896-664-01

RYTARY® (Carbidopa and Levodopa) Extended-Release Capsules

61.25 mg/245 mg

100 Capsules

Rx Only

Amneal Specialty, a division of Amneal Pharmaceuticals LLC